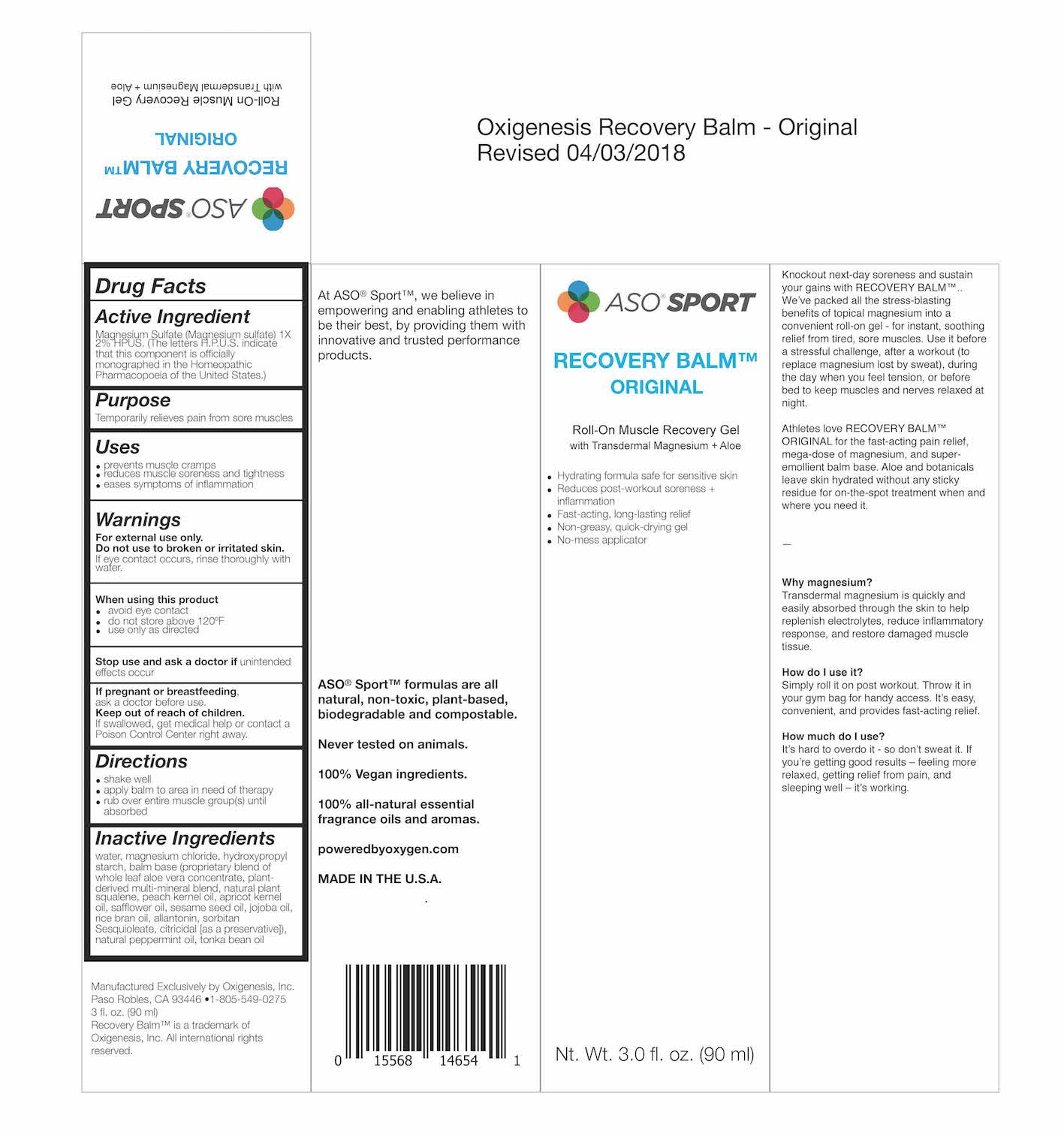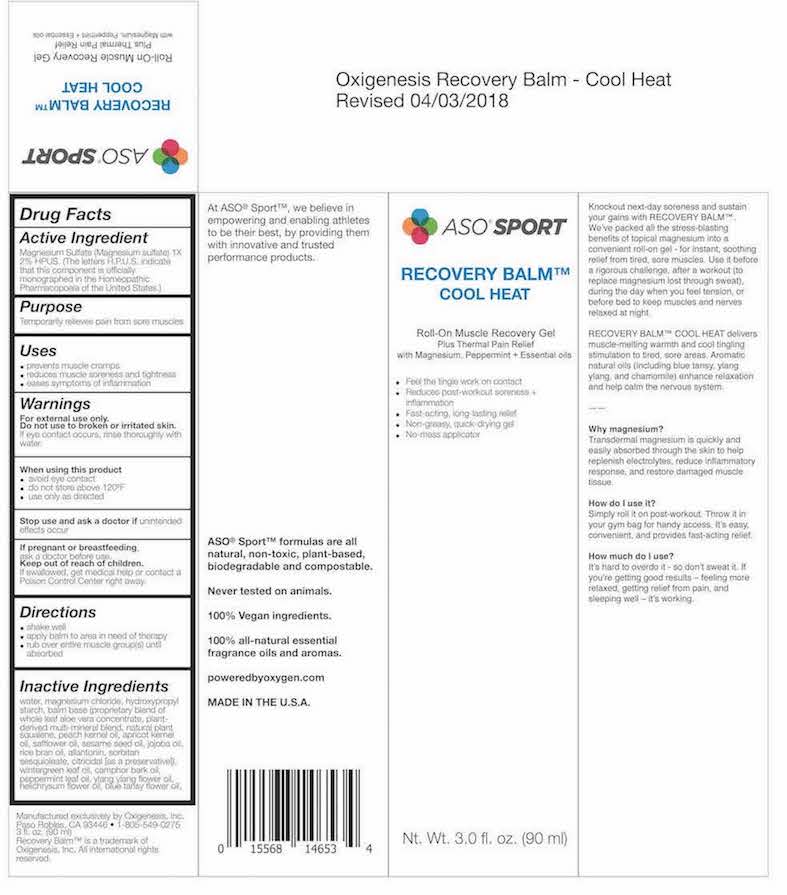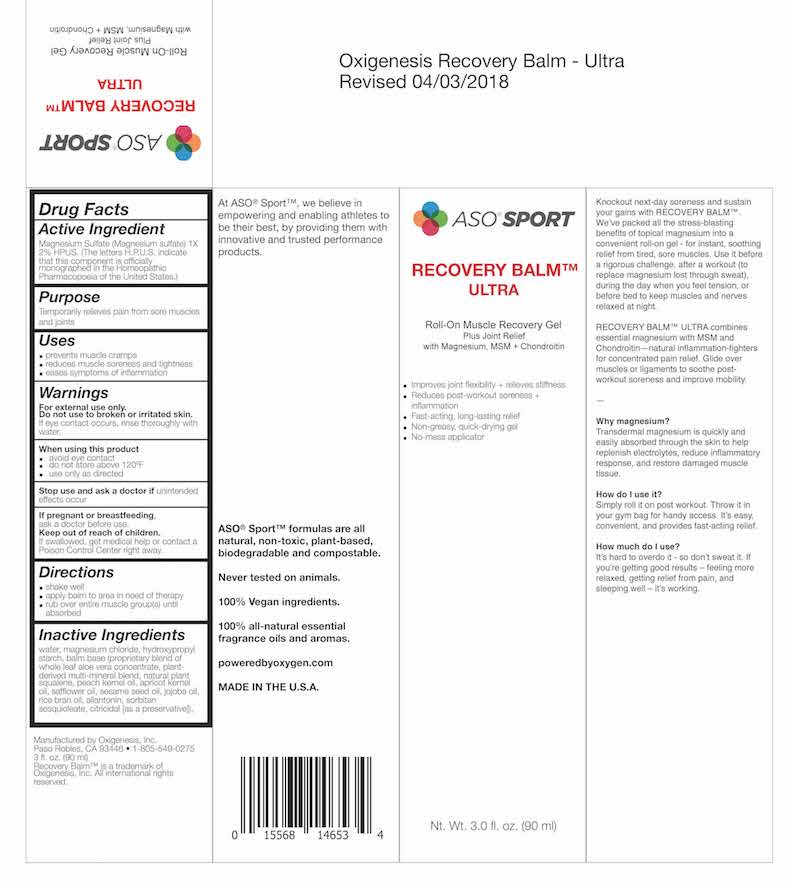 DRUG LABEL: RECOVERY BALM - ORIGINAL
NDC: 72136-002 | Form: GEL
Manufacturer: Oxigenesis, Inc
Category: homeopathic | Type: HUMAN PRESCRIPTION DRUG LABEL
Date: 20180406

ACTIVE INGREDIENTS: MAGNESIUM SULFATE HEPTAHYDRATE 2 [hp_X]/100 mL
INACTIVE INGREDIENTS: ALOE VERA LEAF; SQUALENE; PERSIC OIL; APRICOT KERNEL OIL; SAFFLOWER OIL; SESAME OIL; JOJOBA OIL; ALLANTOIN; CITRUS PARADISI SEED; MAGNESIUM CHLORIDE TETRAHYDRATE; PEPPERMINT OIL; DIPTERYX ODORATA SEED

ROLL ON MUSCLE GEL

RECOVERY BALM COOL HEAT

ROLL ON MUSCULER GEL

WARNINGS

- Do not use on broken or irritated skin
- Avoid eye contact
- Do not store in above 120 F
- Use as directed
- external use only

Precautions

- If pregnant or Breast feeding ask doctor before use
- keep out of reach of children

USES

- Prevent muscles cramp
- Reduse muscles soreness and tightness
- eases muscles symptoms of inflammation

Directions

- Shake well before use
- Apply balm in area need of theropy
- Rub over entire muscles group until absorbed

Inactives

Inactive Ingredient for Recovery Blam Original Product Label

water, magnesium chloride, hydroxypropyl starch, balm base (proprietary blend of whole leaf aloe vera concentrate, plantderived multi-mineral blend, natural plant squalene, peach kernel oil, apricot kernel oil, safflower oil, sesame seed oil, jojoba oil, rice bran oil, allantonin, sorbitan Sesquioleate, citricidal [as a preservative]), natural peppermint oil, tonka bean oil

Inactive Ingredient for Cool Heat

water, magnesium chloride, hydroxypropyl starch, balm base (proprietary blend of whole leaf aloe vera concentrate, plantderived multi-mineral blend, natural plant squalene, peach kernel oil, apricot kernel oil, safflower oil, sesame seed oil, jojoba oil, rice bran oil, allantonin, sorbitan sesquioleate, citricidal [as a preservative]), wintergreen leaf oil, camphor bark oil, peppermint leaf oil, ylang ylang flower oil, helichrysum flower oil, blue tansy flower oil,

Inactive Ingredient for Ultra

water, magnesium chloride, hydroxypropyl starch, balm base (proprietary blend of whole leaf aloe vera concentrate, plantderived multi-mineral blend, natural plant squalene, peach kernel oil, apricot kernel oil, safflower oil, sesame seed oil, jojoba oil, rice bran oil, allantonin, sorbitan sesquioleate, citricidal [as a preservative]), wintergreen leaf oil, camphor bark oil, peppermint leaf oil, ylang ylang flower oil, helichrysum flower oil, blue tansy flower oil,